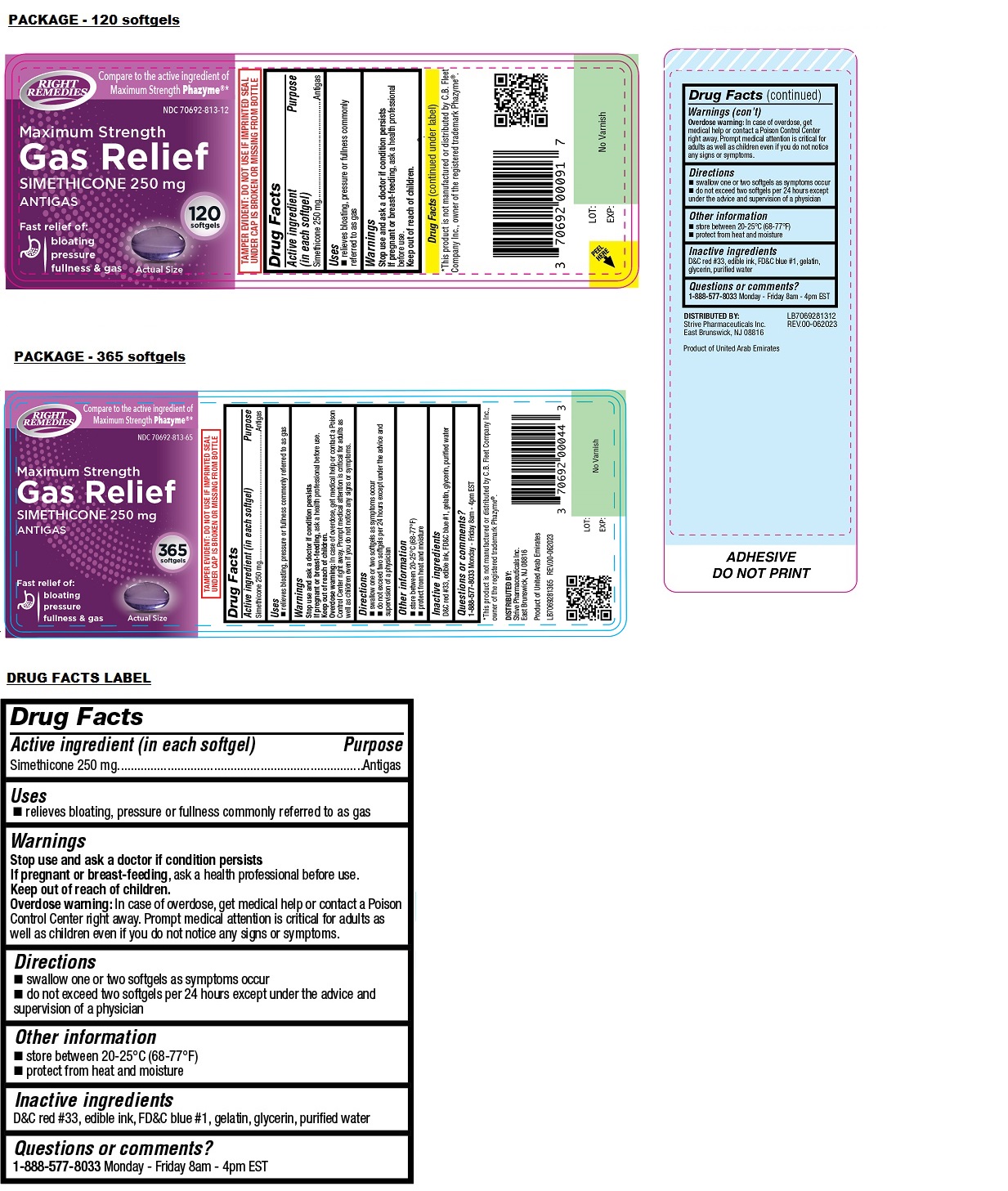 DRUG LABEL: Right Remedies Maximum Strength Gas Relief Softgel
NDC: 70692-813 | Form: CAPSULE, LIQUID FILLED
Manufacturer: Strive Pharmaceuticals Inc.
Category: otc | Type: HUMAN OTC DRUG LABEL
Date: 20240205

ACTIVE INGREDIENTS: DIMETHICONE 250 mg/1 1
INACTIVE INGREDIENTS: D&C RED NO. 33; FD&C BLUE NO. 1; GELATIN, UNSPECIFIED; GLYCERIN; WATER

RIGHT REMEDIES Maximum Strength Gas Relief softgel

Active ingredient (in each softgel)

Simethicone 250 mg

Purpose

Antigas

Uses

• relieves bloating, pressure or fullness commonly referred to as gas

Warnings

Stop use and ask a doctor if condition persists

If pregnant or breast-feeding, ask a health professional before use

Keep out of reach of children.
Overdose warning: In case of overdose, get medical help or contact a Poison Control Center right away. Prompt medical attention is critical for adults as well as children even if you do not notice any signs or symptoms.

Directions

• swallow one or two softgels as symptoms occur
• do not exceed two softgels per 24 hours except under the advice and supervision of a physician

Other information

• store between 20-25°C (68-77°F)
• protect from heat and moisture

Inactive ingredients

D&C red #33, edible ink, FD&C blue #1, gelatin, glycerin, purified water

Questions or comments?

1-888-577-8033 Monday - Friday 8am - 4pm EST

Compare to the active ingredient of Maximum Strength Phazyme®*

Fast relief of:
bloating
pressure
fullness & gas

TAMPER EVIDENT: DO NOT USE IF IMPRINTED SEAL UNDER CAP IS BROKEN OR MISSING FROM BOTTLE

*This product is not manufactured or distributed by C.B. Fleet Company Inc., owner of the registered trademark Phazyme®.

DISTRIBUTED BY:
Strive Pharmaceuticals Inc.
East Brunswick, NJ 08816

Product of United Arab Emirates